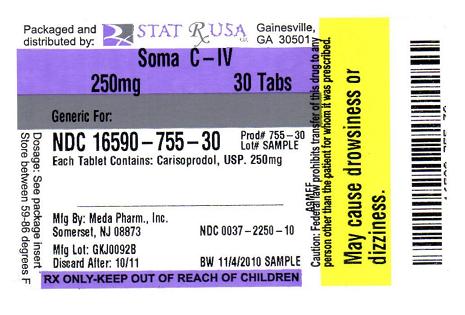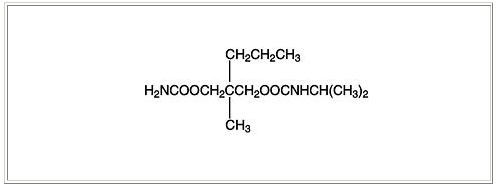 DRUG LABEL: SOMA
NDC: 16590-755 | Form: TABLET
Manufacturer: STAT RX USA LLC
Category: prescription | Type: HUMAN PRESCRIPTION DRUG LABEL
Date: 20110707
DEA Schedule: CIV

ACTIVE INGREDIENTS: CARISOPRODOL 250 mg/1 1
INACTIVE INGREDIENTS: alginic acid; magnesium stearate; potassium sorbate; tribasic calcium phosphate

HIGHLIGHTS OF PRESCRIBING INFORMATION

These highlights do not include all the information needed to use SOMA safely and effectively. See full prescribing information for SOMA.
SOMA (carisoprodol) Tablets for Oral use
Initial U.S. Approval: 1959

RECENT MAJOR CHANGES

Warnings and Precautions, Sedation (5.1) 10/2009

Warnings and Precautions, Drug Dependence, Withdrawal, and Abuse (5.2) 10/2009

1 INDICATIONS AND USAGE

SOMA is indicated for the relief of discomfort associated with acute, painful musculoskeletal conditions. (1)
Important Limitations:

- Should only be used for acute treatment periods up to two or three weeks (1)
- Not recommended in pediatric patients less than 16 years of age (8.4)

2 DOSAGE AND ADMINISTRATION

- Recommended dose is 250 mg to 350 mg three times a day and at bedtime. (2)

3 DOSAGE FORMS AND STRENGTHS

Tablets: 250 mg, 350 mg (3)

4 CONTRAINDICATIONS

- Acute intermittent porphyria (4)
- Hypersensitivity reactions to a carbamate such as meprobamate (4)

5 WARNINGS AND PRECAUTIONS

- Due to sedative properties, may impair ability to perform hazardous tasks such as driving or operating machinery (5.1)
- Additive sedative effects when used with other CNS depressants including alcohol (5.1)
- Cases of Drug Dependence, Withdrawal, and Abuse (5.2)
- Seizures (5.3)

6 ADVERSE REACTIONS

Most common adverse reactions (incidence > 2%) are drowsiness, dizziness, and headache (6.1)

To report SUSPECTED ADVERSE REACTIONS, contact Meda Pharmaceuticals Inc. at 1-800-526-3840 or FDA at 1-800-FDA-1088 or www.fda.gov/medwatch.

7 DRUG INTERACTIONS

- CNS depressants (e.g., alcohol, benzodiazepines, opioids, tricyclic antidepressants) - additive sedative effects (5.1 and 7.1)

FULL PRESCRIBING INFORMATION

1 INDICATIONS AND USAGE

SOMA is indicated for the relief of discomfort associated with acute, painful musculoskeletal conditions in adults.
SOMA should only be used for short periods (up to two or three weeks) because adequate evidence of effectiveness for more prolonged use has not been established and because acute, painful musculoskeletal conditions are generally of short duration [see Dosage and Administration (2)].

2 DOSAGE AND ADMINISTRATION

The recommended dose of SOMA is 250 mg to 350 mg three times a day and at bedtime. The recommended maximum duration of SOMA use is up to two or three weeks.

3 DOSAGE FORMS AND STRENGTHS

250mg Tablets: round, convex, white tablets, inscribed with SOMA 250

350mg Tablets: round, convex, white tablets, inscribed with SOMA 350

4 CONTRAINDICATIONS

SOMA is contraindicated in patients with a history of acute intermittent porphyria or a hypersensitivity reaction to a carbamate such as meprobamate.

5 WARNINGS AND PRECAUTIONS

5.1 Sedation

SOMA has sedative properties (in the low back pain trials, 13% to 17% of patients who received SOMA experienced sedation compared to 6% of patients who received placebo) [see ADVERSE REACTIONS (6.1)] and may impair the mental and/or physical abilities required for the performance of potentially hazardous tasks such as driving a motor vehicle or operating machinery. There have been post-marketing reports of motor vehicle accidents associated with the use of SOMA.

Since the sedative effects of SOMA and other CNS depressants (e.g., alcohol, benzodiazepines, opioids, tricyclic antidepressants) may be additive, appropriate caution should be exercised with patients who take more than one of these CNS depressants simultaneously.

5.2 Drug Dependence, Withdrawal, and Abuse

In the postmarketing experience with SOMA, cases of dependence, withdrawal, and abuse have been reported with prolonged use. Most cases of dependence, withdrawal, and abuse occurred in patients who have had a history of addiction or who used SOMA in combination with other drugs with abuse potential. However, there have been post-marketing adverse event reports of SOMA-associated abuse when used without other drugs with abuse potential. Withdrawal symptoms have been reported following abrupt cessation after prolonged use. To reduce the chance of SOMA dependence, withdrawal, or abuse, SOMA should be used with caution in addiction-prone patients and in patients taking other CNS depressants including alcohol, and SOMA should not be used more than two to three weeks for the relief of acute musculoskeletal discomfort.

SOMA, and one of its metabolites, meprobamate (a controlled substance), may cause dependence [see Clinical Pharmacology (12.3)].

5.3 Seizures

There have been postmarketing reports of seizures in patients who received SOMA. Most of these cases have occurred in the setting of multiple drug overdoses (including drugs of abuse, illegal drugs, and alcohol) [see Overdosage (10)].

6 ADVERSE REACTIONS

6.1 Clinical Studies Experience

Because clinical studies are conducted under widely varying conditions, adverse reaction rates observed in clinical studies of a drug cannot be directly compared to rates in the clinical studies of another drug and may not reflect rates observed in practice.

The data described below are based on 1387 patients pooled from two double blind, randomized, multicenter, placebo controlled, one-week trials in adult patients with acute, mechanical, lower back pain [see Clinical Studies (14)]. In these studies, patients were treated with 250 mg of SOMA, 350 mg of SOMA, or placebo three times a day and at bedtime for seven days. The mean age was about 41 years old with 54% females and 46% males and 74 % Caucasian, 16 % Black, 9% Asian, and 2% other.

There were no deaths and there were no serious adverse reactions in these two trials. In these two studies, 2.7%, 2%, and 5.4%, of patients treated with placebo, 250 mg of SOMA, and 350 mg of SOMA, respectively, discontinued due to adverse events; and 0.5%, 0.5%, and 1.8% of patients treated with placebo, 250 mg of SOMA, and 350 mg of SOMA, respectively, discontinued due to central nervous system adverse reactions.

Table 1 displays adverse reactions reported with frequencies greater than 2% and more frequently than placebo in patients treated with SOMA in the two trials described above.

Table 1. Patients with Adverse Reactions in Controlled Studies
Adverse Reaction | Placebo (n=560) n (%) | SOMA 250 mg (n=548) n (%) | SOMA 350 mg (n=279) n (%)
Drowsiness | 31 (6) | 73 (13) | 47 (17)
Dizziness | 11 (2) | 43 (8) | 19 (7)
Headache | 11 (2) | 26 (5) | 9 (3)

6.2 Postmarketing Experience

The following events have been reported during postapproval use of SOMA. Because these reactions are reported voluntarily from a population of uncertain size, it is not always possible to reliably estimate their frequency or establish a causal relationship to drug exposure.

Cardiovascular: Tachycardia, postural hypotension, and facial flushing [see Overdosage (10)].
Central Nervous System: Drowsiness, dizziness, vertigo, ataxia, tremor, agitation, irritability, headache, depressive reactions, syncope, insomnia, and seizures [see Overdosage (10)].
Gastrointestinal: Nausea, vomiting, and epigastric discomfort.
Hematologic: Leukopenia, pancytopenia

7 DRUG INTERACTIONS

7.1 CNS Depressants

The sedative effects of SOMA and other CNS depressants (e.g., alcohol, benzodiazepines, opioids, tricyclic antidepressants) may be additive. Therefore, caution should be exercised with patients who take more than one of these CNS depressants simultaneously. Concomitant use of SOMA and meprobamate, a metabolite of SOMA, is not recommended [see Warnings and Precautions (5.1)].

7.2 CYP2C19 Inhibitors and Inducers

Carisoprodol is metabolized in the liver by CYP2C19 to form meprobamate [see Clinical Pharmacology (12.3) ]. Co-administration of CYP2C19 inhibitors, such as omeprazole or fluvoxamine, with SOMA could result in increased exposure of carisoprodol and decreased exposure of meprobamate. Co-administration of CYP2C19 inducers, such as rifampin or St. John’s Wort, with SOMA could result in decreased exposure of carisoprodol and increased exposure of meprobamate. Low dose aspirin also showed an induction effect on CYP2C19. The full pharmacological impact of these potential alterations of exposures in terms of either efficacy or safety of SOMA is unknown.

8 USE IN SPECIFIC POPULATIONS

8.1 Pregnancy: Pregnancy Category C.

There are no data on the use of SOMA during human pregnancy. Animal studies indicate that carisoprodol crosses the placenta and results in adverse effects on fetal growth and postnatal survival. The primary metabolite of carisoprodol, meprobamate, is an approved anxiolytic. Retrospective, post-marketing studies do not show a consistent association between maternal use of meprobamate and an increased risk for particular congenital malformations.

Teratogenic effects: Animal studies have not adequately evaluated the teratogenic effects of carisoprodol. There was no increase in the incidence of congenital malformations noted in reproductive studies in rats, rabbits, and mice treated with meprobamate. Retrospective, post-marketing studies of meprobamate during human pregnancy were equivocal for demonstrating an increased risk of congenital malformations following first trimester exposure. Across studies that indicated an increased risk, the types of malformations were inconsistent.

Nonteratogenic effects: In animal studies, carisoprodol reduced fetal weights, postnatal weight gain, and postnatal survival at maternal doses equivalent to 1-1.5 times the human dose (based on a body surface area comparison). Rats exposed to meprobamate in-utero showed behavioral alterations that persisted into adulthood. For children exposed to meprobamate in-utero, one study found no adverse effects on mental or motor development or IQ scores. SOMA should be used during pregnancy only if the potential benefit justifies the risk to the fetus.

8.2 Labor and Delivery

There is no information about the effects of SOMA on the mother and the fetus during labor and delivery.

8.3 Nursing Mothers

Very limited data in humans show that SOMA is present in breast milk and may reach concentrations two to four times the maternal plasma concentrations. In one case report, a breast-fed infant received about 4-6% of the maternal daily dose through breast milk and experienced no adverse effects. However, milk production was inadequate and the baby was supplemented with formula. In lactation studies in mice, female pup survival and pup weight at weaning were decreased. This information suggests that maternal use of SOMA may lead to reduced or less effective infant feeding (due to sedation) and/or decreased milk production. Caution should be exercised when SOMA is administered to a nursing woman.

8.4 Pediatric Use

The efficacy, safety, and pharmacokinetics of SOMA in pediatric patients less than 16 years of age have not been established.

8.5 Geriatric Use

The efficacy, safety, and pharmacokinetics of SOMA in patients over 65 years old have not been established.

8.6 Renal Impairment

The safety and pharmacokinetics of SOMA in patients with renal impairment have not been evaluated. Since SOMA is excreted by the kidney, caution should be exercised if SOMA is administered to patients with impaired renal function. Carisoprodol is dialyzable by hemodialysis and peritoneal dialysis.

8.7 Hepatic Impairment

The safety and pharmacokinetics of SOMA in patients with hepatic impairment have not been evaluated. Since SOMA is metabolized in the liver, caution should be exercised if SOMA is administered to patients with impaired hepatic function.

8.8 Patients with Reduced CYP2C19 Activity

Patients with reduced CYP2C19 activity have higher exposure to carisoprodol. Therefore, caution should be exercised in administration of SOMA to these patients [ see Clinical Pharmacology (12.3)].

9 DRUG ABUSE AND DEPENDENCE

SOMA is not a controlled substance [see Warnings and Precautions (5.2) ]. Discontinuation of carisoprodol in animals or in humans after chronic administration can produce withdrawal signs, and there are published case reports of human carisoprodol dependence.

In vitro studies demonstrate that carisoprodol elicits barbiturate-like effects. Animal behavioral studies indicate that carisoprodol produces rewarding effects. Monkeys self administer carisoprodol. Drug discrimination studies using rats indicate that carisoprodol has positive reinforcing and discriminative effects similar to barbital, meprobamate, and chlordiazepoxide.

10 OVERDOSAGE

Overdosage of SOMA commonly produces CNS depression. Death, coma, respiratory depression, hypotension, seizures, delirium, hallucinations, dystonic reactions, nystagmus, blurred vision, mydriasis, euphoria, muscular incoordination, rigidity, and/or headache have been reported with SOMA overdosage. Many of the SOMA overdoses have occurred in the setting of multiple drug overdoses (including drugs of abuse, illegal drugs, and alcohol). The effects of an overdose of SOMA and other CNS depressants (e.g., alcohol, benzodiazepines, opioids, tricyclic antidepressants) can be additive even when one of the drugs has been taken in the recommended dosage. Fatal accidental and non-accidental overdoses of SOMA have been reported alone or in combination with CNS depressants.

Treatment of Overdosage: Basic life support measures should be instituted as dictated by the clinical presentation of the SOMA overdose. Induced emesis is not recommended due to the risk of CNS and respiratory depression, which may increase the risk of aspiration pneumonia. Gastric lavage should be considered soon after ingestion (within one hour). Circulatory support should be administered with volume infusion and vasopressor agents if needed. Seizures should be treated with intravenous benzodiazepines and the reoccurrence of seizures may be treated with phenobarbital. In cases of severe CNS depression, airway protective reflexes may be compromised and tracheal intubation should be considered for airway protection and respiratory support.

The following types of treatment have been used successfully with an overdose of meprobamate, a metabolite of SOMA: activated charcoal (oral or via nasogastric tube), forced diuresis, peritoneal dialysis, and hemodialysis (carisoprodol is also dialyzable). Careful monitoring of urinary output is necessary and overhydration should be avoided. Observe for possible relapse due to incomplete gastric emptying and delayed absorption. For more information on the management of an overdose of SOMA, contact a Poison Control Center.

11 DESCRIPTION

SOMA (carisoprodol) Tablets are available as 250 mg and 350 mg round, white tablets. Carisoprodol is a white, crystalline powder, having a mild, characteristic odor and a bitter taste. It is slightly soluble in water; freely soluble in alcohol, in chloroform, and in acetone; and its solubility is practically independent of pH. Carisoprodol is present as a racemic mixture. Chemically, carisoprodol is N-isopropyl-2-methyl-2-propyl-1,3-propanediol dicarbamate and the molecular formula is C12H24N2O4, with a molecular weight of 260.33. The structural formula is:

Other ingredients in the SOMA drug product include alginic acid, magnesium stearate, potassium sorbate, starch, and tribasic calcium phosphate.

12 CLINCIAL PHARMACOLOGY

12.1 Mechanism of Action

The mechanism of action of carisoprodol in relieving discomfort associated with acute painful musculoskeletal conditions has not been clearly identified.

In animal studies, muscle relaxation induced by carisoprodol is associated with altered interneuronal activity in the spinal cord and in the descending reticular formation of the brain.

12.2 Pharmacodynamics

Carisoprodol is a centrally acting skeletal muscle relaxant that does not directly relax skeletal muscles.

A metabolite of carisoprodol, meprobamate, has anxiolytic and sedative properties. The degree to which these properties of meprobamate contribute to the safety and efficacy of SOMA is unknown.

12.3 Pharmacokinetics

The pharmacokinetics of carisoprodol and its metabolite meprobamate were studied in a crossover study of 24 healthy subjects (12 male and 12 female) who received single doses of 250 mg and 350 mg SOMA (see Table 2). The exposure of carisoprodol and meprobamate was dose proportional between the 250 mg and 350 mg doses. The Cmax of meprobamate was 2.5 ± 0.5 μg/mL (mean ± SD) after administration of a single 350 mg dose of SOMA, which is approximately 30% of the Cmax of meprobamate (approximately 8 μg/mL) after administration of a single 400 mg dose of meprobamate.

Table 2. Pharmacokinetic Parameters of Carisoprodol and Meprobamate (Mean ± SD, n=24)
 | 250 mg SOMA | 350 mg SOMA
 | Carisoprodol
Cmax (μg/mL) | 1.2 ± 0.5 | 1.8 ± 1.0
AUCinf (μg*hr/mL) | 4.5 ± 3.1 | 7.0 ± 5.0
Tmax (hr) | 1.5 ± 0.8 | 1.7 ± 0.8
T1/2 (hr) | 1.7 ± 0.5 | 2.0 ± 0.5
 | Meprobamate
Cmax (μg/mL) | 1.8 ± 0.3 | 2.5 ± 0.5
AUCinf (μg*hr/mL) | 32 ± 6.2 | 46 ± 9.0
Tmax (hr) | 3.6 ± 1.7 | 4.5 ± 1.9
T1/2 (hr) | 9.7 ± 1.7 | 9.6 ± 1.5

Absorption: Absolute bioavailability of carisoprodol has not been determined. The mean time to peak plasma concentrations (Tmax) of carisoprodol was approximately 1.5 to 2 hours. Co-administration of a high-fat meal with SOMA (350 mg tablet) had no effect on the pharmacokinetics of carisoprodol. Therefore, SOMA may be administered with or without food.

Metabolism: The major pathway of carisoprodol metabolism is via the liver by cytochrome enzyme CYP2C19 to form meprobamate. This enzyme exhibits genetic polymorphism (see Patients with Reduced CYP2C19 Activity below).

Elimination: Carisoprodol is eliminated by both renal and non-renal routes with a terminal elimination half-life of approximately 2 hours. The half-life of meprobamate is approximately 10 hours.

Gender: Exposure of carisoprodol is higher in female than in male subjects (approximately 30-50% on a weight adjusted basis). Overall exposure of meprobamate is comparable between female and male subjects.

Patients with Reduced CYP2C19 Activity: SOMA should be used with caution in patients with reduced CYP2C19 activity. Published studies indicate that patients who are poor CYP2C19 metabolizers have a 4-fold increase in exposure to carisoprodol, and concomitant 50% reduced exposure to meprobamate compared to normal CYP2C19 metabolizers. The prevalence of poor metabolizers in Caucasians and African Americans is approximately 3-5% and in Asians is approximately 15-20%.

13 NONCLINICAL TOXICOLOGY

13.1 Carcinogenesis, Mutagenesis, Impairment of Fertility

Long term studies in animals have not been performed to evaluate the carcinogenic potential of carisoprodol.

SOMA was not formally evaluated for genotoxicity. In published studies, carisoprodol was mutagenic in the in vitro mouse lymphoma cell assay in the absence of metabolizing enzymes, but was not mutagenic in the presence of metabolizing enzymes. Carisoprodol was clastogenic in the in vitro chromosomal aberration assay using Chinese hamster ovary cells with or without the presence of metabolizing enzymes. Other types of genotoxic tests resulted in negative findings. Carisoprodol was not mutagenic in the Ames reverse mutation assay using S. typhimurium strains with or without metabolizing enzymes, and was not clastogenic in an in vivo mouse micronucleus assay of circulating blood cells.

SOMA was not formally evaluated for effects on fertility. Published reproductive studies of carisoprodol in mice found no alteration in fertility although an alteration in reproductive cycles characterized by a greater time spent in estrus was observed at a carisoprodol dose of 1200 mg/kg/day. In a 13-week toxicology study that did not determine fertility, mouse testes weight and sperm motility were reduced at a dose of 1200 mg/kg/day. In both studies, the no effect level was 750 mg/kg/day, corresponding to approximately 2.6 times the human equivalent dosage of 350 mg four times a day, based on a body surface area comparison. The significance of these findings for human fertility is not known.

14 CLINICAL STUDIES

The safety and efficacy of SOMA for the relief of acute, idiopathic mechanical low back pain was evaluated in two, 7-day, double blind, randomized, multicenter, placebo controlled, U.S. trials (Studies 1 and 2). Patients had to be 18 to 65 years old and had to have acute back pain (≤ 3 days of duration) to be included in the trials. Patients with chronic back pain; at increased risk for vertebral fracture (e.g., history of osteoporosis); with a history of spinal pathology (e.g., herniated nucleus pulposis, spondylolisthesis or spinal stenosis); with inflammatory back pain, or with evidence of a neurologic deficit were excluded from participation. Concomitant use of analgesics (e.g., acetaminophen, NSAIDs, tramadol, opioid agonists), other muscle relaxants, botulinum toxin, sedatives (e.g., barbiturates, benzodiazepines, promethazine hydrochloride), and anti-epileptic drugs was prohibited.

In Study 1, patients were randomized to one of three treatment groups (i.e., SOMA 250 mg, SOMA 350 mg, or placebo) and in Study 2 patients were randomized to two treatment groups (i.e., SOMA 250 mg or placebo). In both studies, patients received study medication three times a day and at bedtime for seven days.

The primary endpoints were the relief from starting backache and the global impression of change, as reported by patients, on Study Day 3. Both endpoints were scored on a 5-point rating scale from 0 (worst outcome) to 4 (best outcome) in both studies. The primary statistical comparison was between the SOMA 250 mg and placebo groups in both studies.

The proportion of patients who used concomitant acetaminophen, NSAIDs, tramadol, opioid agonists, other muscle relaxants, and benzodiazepines was similar in the treatment groups.

The results for the primary efficacy evaluations in the acute, low back pain studies are presented in Table 3.

Table 3. Results of the Primary Efficacy Endpointsa in Studies 1 and 2
Study | Parameter | Placebo | SOMA 250 mg | SOMA 350 mg
 | Number of Patients | n=269 | n=264 | n=273
 | Relief from Starting Backache, Mean (SE) b | 1.4 (0.1) | 1.8 (0.1) | 1.8 (0.1)
1 | Difference between SOMA and Placebo, Mean (SE) b (95% CI) |  | 0.4 (0.2, 0.5) | 0.4 (0.2, 0.6)
 | Global Impression of Change, Mean (SE) b | 1.9 (0.1) | 2.2 (0.1) | 2.2 (0.1)
 | Difference between SOMA and Placebo, Mean (SE) b (95% CI) |  | 0.2 (0.1, 0.4) | 0.3 (0.1, 0.4)
 | Number of Patients | n=278 | n=269
 | Relief from Starting Backache, Mean (SE) b | 1.1 (0.1) | 1.8 (0.1)
2 | Difference between SOMA and Placebo, Mean (SE) b (95% CI) |  | 0.7 (0.5, 0.9)
 | Global Impression of Change, Mean (SE) b | 1.7 (0.1) | 2.2 (0.1)
 | Difference between SOMA and Placebo, Mean (SE) b (95% CI) |  | 0.5 (0.4, 0.7)
a The primary efficacy endpoints (Relief from Starting Backache and Global Impression of Change) were assessed by the patients on Study Day 3. These endpoints were scored on a 5-point rating scale from 0 (worst outcome) to 4 (best outcome).
b Mean is the least squared mean and SE is the standard error of the mean. The ANOVA model was used for the primary statistical comparison between the SOMA 250 mg and placebo groups.

Patients treated with SOMA experienced improvement in function as measured by the Roland-Morris Disability Questionnaire (RMDQ) score on Days 3 and 7.

16 HOW SUPPLIED/STORAGE AND HANDLING

250mg Tablets: round, convex, white tablets, inscribed with SOMA 250; available in bottles of 100 (NDC 0037-2250-10) and bottles of 30 (NDC 0037-2250-30).

350mg Tablets: round, convex, white tablets, inscribed with SOMA 350; available in bottles of 100 (NDC 0037-2001-01).

Storage:
Store at controlled room temperature 20° - 25°C (68° - 77°F).

17 PATIENT COUNSELING INFORMATION

Patients should be advised to contact their physician if they experience any adverse reactions to SOMA.

17.1 Sedation

Patients should be advised that SOMA may cause drowsiness and/or dizziness, and has been associated with motor vehicle accidents. Patients should be advised to avoid taking SOMA before engaging in potentially hazardous activities such as driving a motor vehicle or operating machinery [see Warnings and Precautions (5.1)].

17.2 Avoidance of Alcohol and Other CNS Depressants

Patients should be advised to avoid alcoholic beverages while taking SOMA and to check with their doctor before taking other CNS depressants such as benzodiazepines, opioids, tricyclic antidepressants, sedating antihistamines, or other sedatives [see Warnings and Precautions (5.1)].

17.3 SOMA Should Only Be Used for Short-Term Treatment

Patients should be advised that treatment with SOMA should be limited to acute use (up to two or three weeks) for the relief of acute, musculoskeletal discomfort. In the post-marketing experience with SOMA, cases of dependence, withdrawal, and abuse have been reported with prolonged use. If the musculoskeletal symptoms still persist, patients should contact their healthcare provider for further evaluation.

To report SUSPECTED ADVERSE REACTIONS, contact Meda Pharmaceuticals Inc. at 1-800-526-3840 or FDA at 1-800-FDA-1088 or www.fda.gov/medwatch.

Meda Pharmaceuticals
Meda Pharmaceuticals Inc.
Somerset, New Jersey 08873-4120

IN-090H2-18 Rev. 10/09